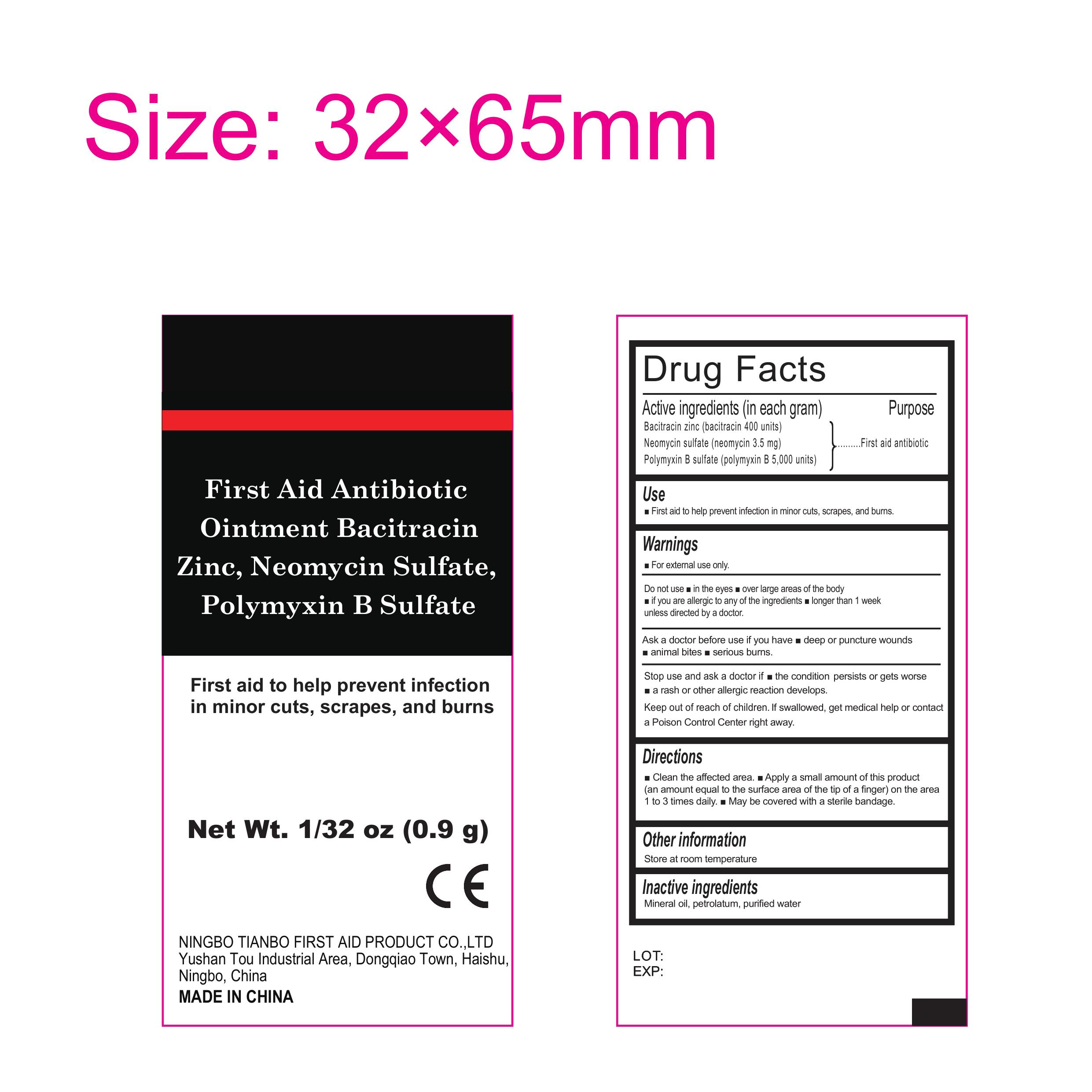 DRUG LABEL: First Aid Antibiotic
NDC: 73288-005 | Form: OINTMENT
Manufacturer: NINGBO TIANBO FIRST AID PRODUCT CO., LTD.
Category: otc | Type: HUMAN OTC DRUG LABEL
Date: 20241129

ACTIVE INGREDIENTS: BACITRACIN ZINC 400 [USP'U]/1 g; NEOMYCIN SULFATE 0.0035 g/1 g; POLYMYXIN B SULFATE 5000 [USP'U]/1 g
INACTIVE INGREDIENTS: MINERAL OIL; WATER; PETROLATUM

73288-005

Active Ingredient:

Bacitracin Zinc: 400 Units

Neomycin Sulfate: 3.5 mg

Polymyxin B Sulfate: 5000 Units

Purpose: First Aid Antibiotic

Uses:

First aid to help prevent infections in minor cuts, scrapes, and burns

Warnings:

For external use only

Do not use

- in eyes
- over large areas of the bogy
- if you are allergic to any of the ingredients
- longer than one week

unless you are directed by the doctor

Ask a doctor before use if you have

- deep or puncture wounds
- animal bites
- serious burns

Stop use and ask a doctor if

- condition persists ot gets worse
- a rash or other allergic reaction develops

Keep out of reach of children. If swallowed, get medical help or contact a Poison Control Center right away

Directions:

- Clean the affected area
- Apply a small amount of this product (the amount equal to the surface area of the tip of a finger) on the area one to three times daily
- May be covered with a sterile bandage

Other information

- Store at room temperature

Inactive Ingredient

Mineral Oil, Petrplatum, Purified Water